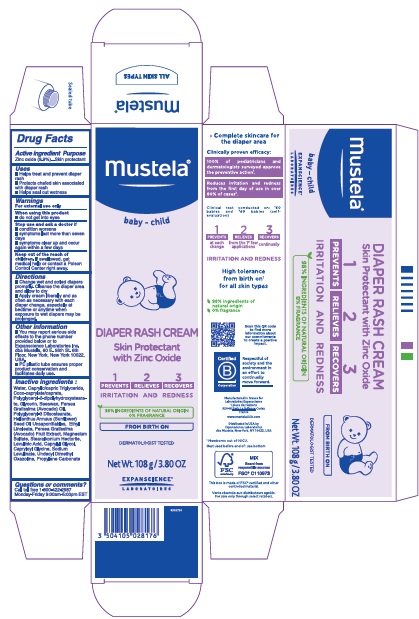 DRUG LABEL: MUSTELA Diaper Rash 1 2 3
NDC: 64768-2922 | Form: CREAM
Manufacturer: Expanscience Laboratories d/b/a Mustela
Category: otc | Type: HUMAN OTC DRUG LABEL
Date: 20241202

ACTIVE INGREDIENTS: ZINC OXIDE 9.9 g/100 g
INACTIVE INGREDIENTS: SUNFLOWER OIL; LEVULINIC ACID; MAGNESIUM SULFATE, UNSPECIFIED FORM; AVOCADO; AVOCADO OIL; POLYGLYCERYL-2 DIPOLYHYDROXYSTEARATE; POLYGLYCERYL-3 DIISOSTEARATE; PROPYLENE CARBONATE; SODIUM LEVULINATE; STEARALKONIUM HECTORITE; 4,4-DIMETHYLOXAZOLIDINE; WATER; YELLOW WAX; MEDIUM-CHAIN TRIGLYCERIDES; CAPRYLOYL GLYCINE; CAPRYLYL GLYCOL; COCO-CAPRYLATE/CAPRATE; ETHYL LINOLEATE; GLYCERIN

MUSTELA® Diaper Rash Cream 1 2 3

Active ingredient

Zinc Oxide 9.9 %

Purpose

skin protectant

Uses

- Helps treat and prevent diaper rash
- Protects chafed skin associated with diaper rash
- Helps seal out wetness

Warnings

For external use only.

When using this product

- do not get into eyes

Stop use and ask a doctor if

- condition worsens
- symptoms last more than seven days
- symptoms clear up and occur again within a few days

Keep out of reach of children.

If swallowed, get medical help or contact a Poison Control Center right away.

Directions

- Change wet and soiled diapers promptly. Cleanse the diaper area and allow to dry.
- Apply cream liberally and as often as necessary and with each diaper change, especially at bedtime or anytime when exposure to wet diapers may be prolonged.

Other information

- You may report serious side effects to the phone number provided below or to Expanscience Laboratories Inc. dba Mustela, 60 E. 56th St. 6th Floor, New York, New York 10022, USA.
- PE plastic tube ensures proper product conservation and facilitates daily use.

Inactive ingredients

Water, Caprylic/capric Triglyceride, Coco-caprylate/caprate, Polyglyceryl-2-dipolyhydroxystearate, Glycerin, Beeswax, Persea Gratissima (Avocado) Oil, Polyglyceryl-3 Diisostearate, Helianthus Annuus (Sunflower) Seed Oil Unsaponifiables, Ethyl Linoleate, Persea Gratissima (Avocado) Fruit Extract, Magnesium Sulfate, Stearalkonium Hectorite, Levulinic Acid, Caprylyl Glycol, Capryloyl Glycine, Sodium Levulinate, Undecyl Dimethyl Oxazoline, Propylene Carbonate

Questions or comments ?

Call toll free 1-800-422-2987 Monday-Friday 9:00am-5:00pm EST

Company information

Distributed in USA by
Expanscience Laboratories
dba Mustela, New York, NY 10022, USA